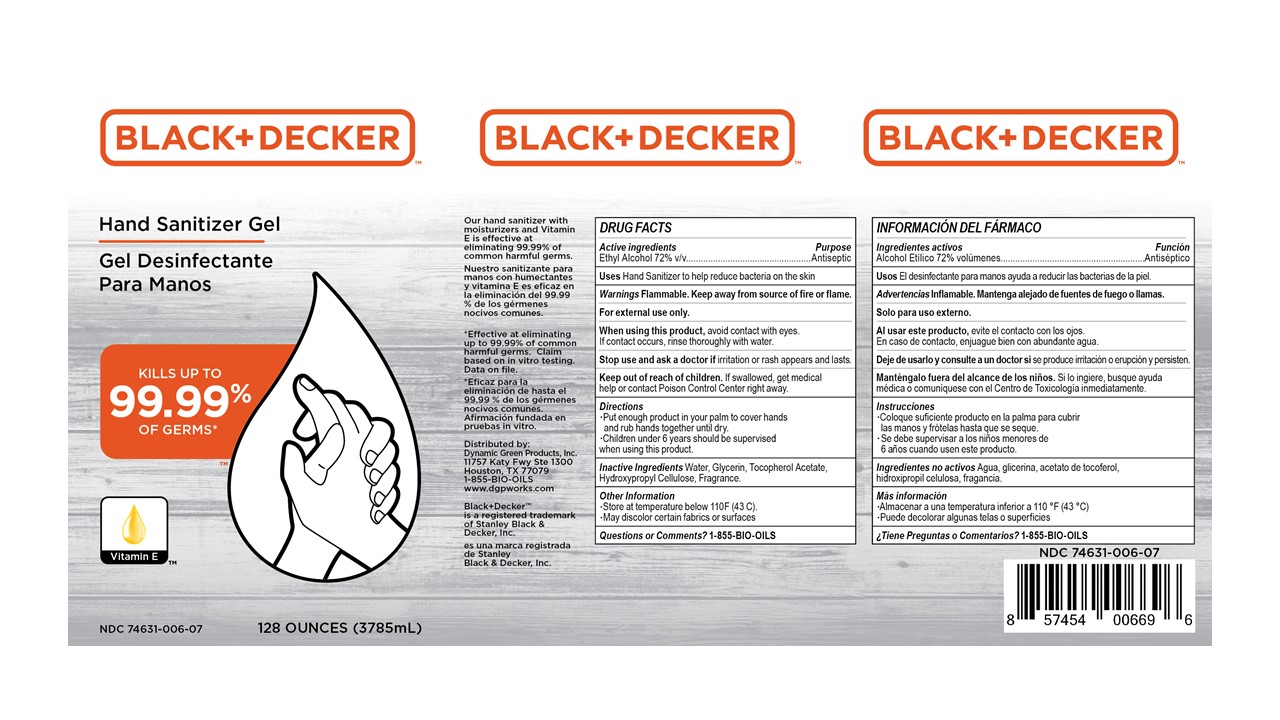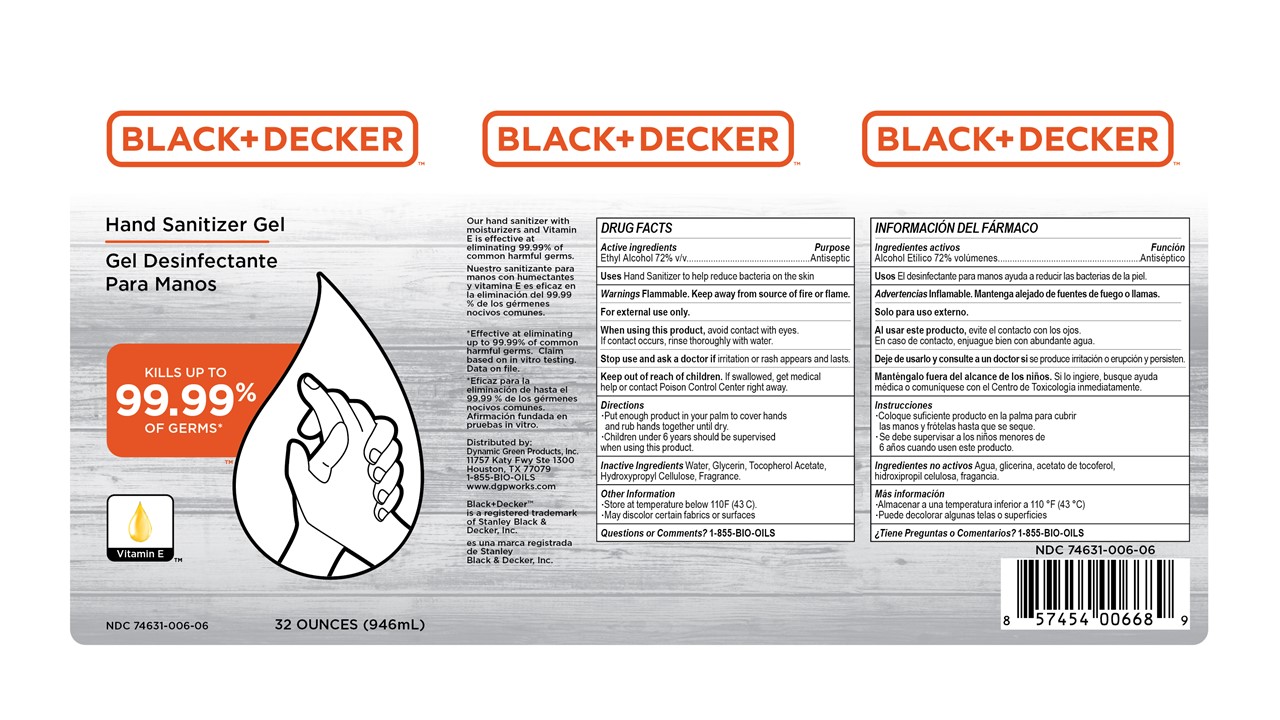 DRUG LABEL: Black Decker Hand Sanitizer Gel
NDC: 74631-006 | Form: GEL
Manufacturer: Dynamic Green Products, Inc.
Category: otc | Type: HUMAN OTC DRUG LABEL
Date: 20200729

ACTIVE INGREDIENTS: ALCOHOL 72 mL/100 mL
INACTIVE INGREDIENTS: WATER; GRAPEFRUIT OIL; HYDROXYPROPYL CELLULOSE (110000 WAMW); ALPHA-TOCOPHEROL ACETATE; GLYCERIN

Drug Facts

Active ingredient

Ethyl Alcohol 72%

Purpose

Antiseptic

INDICATIONS AND USAGE

Hand Sanitizer to help reduce bacteria on the skin

WARNINGS

For external use only

Flammable: Keep away from heat and flame

WHEN USING

* Avoid contact with eyes. If contact occurs flush eyes thoroughly with clean and cool water

* Do not ingest or inhale

Stop use and ask a doctor

* If irritation or rash appears and lasts.

Stop use

* If irritation or redness develops

Keep out of reach of children

* If swallowed, get medical help or contact a Poison Control Center right away.

Directions

* Put enough product in you palm to cover hands and rub hands together until dry.

* Children under 6 years should be supervised when using this product.

Inactive ingredients

Water, Glycerin, Tocopheryl Acetate (Vitamin E), Hydroxypropyl Cellulose, Fragrance

Principal Display Panel

Black+Decker Hand Sanitizer Gel

Kills up to 99.99% of Germs

Vitamin E

Our hand sanitizer with moisturizers and Vitamin E is effective at eliminating 99.99% of common harmful germs.

*Effective at eliminating up to 99.99% of commmon harmful germs. Claim based on in vitro testing. Data on file.

Distributed by:

Dynamic Green Products, Inc.

11757 Katy Fwy Ste 1300

Houston, TX 77079

1-855-BIO-OILS

www.dgpworks.com

Black_Decker is a registered trademark of Stanley Black & Decker, Inc.

XX oz (zzzmL) NDC 74631-006-xx